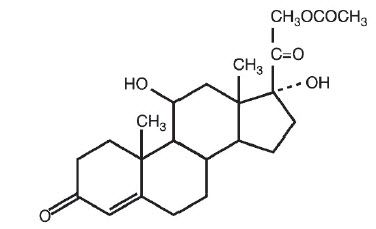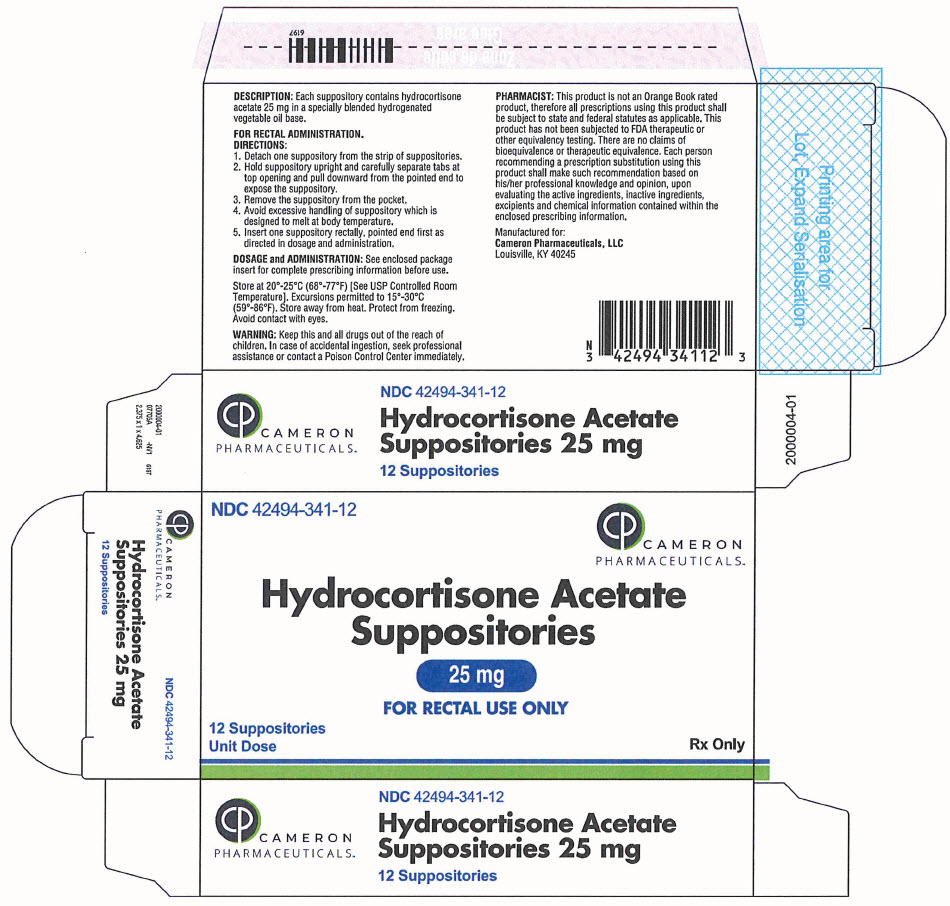 DRUG LABEL: Hydrocortisone Acetate
NDC: 42494-341 | Form: SUPPOSITORY
Manufacturer: Cameron Pharmaceuticals, Limited Liability Company
Category: prescription | Type: HUMAN PRESCRIPTION DRUG LABEL
Date: 20250211

ACTIVE INGREDIENTS: Hydrocortisone Acetate 25 mg/1 1
INACTIVE INGREDIENTS: C10-18 TRIGLYCERIDES

Hydrocortisone Acetate Suppositories, 25 mg

For Rectal Administration

Rx only

DESCRIPTION

Hydrocortisone acetate is a corticosteroid designed chemically as pregn-4-ene-3, 20-dione, 21-(acetyloxy)-11, 17-dihydroxy-(11β) with the following structural formula:

Each suppository for rectal administration contains hydrocortisone acetate, USP 25 mg in a specially blended hydrogenated vegetable base.

CLINICAL PHARMACOLOGY

In normal subjects, about 26% of hydrocortisone acetate is absorbed when the hydrocortisone acetate suppository is applied to the rectum. Absorption of hydrocortisone acetate may vary across abraded or inflamed surfaces.

Topical steroids are primarily effective because of their anti-inflammatory, anti-pruritic and vasoconstrictive action.

INDICATIONS AND USAGE

Hydrocortisone acetate suppositories are indicated for use in inflamed hemorrhoids, post-irradiation (factitial) proctitis, as an adjunct in the treatment of chronic ulcerative colitis, cryptitis, other inflammatory conditions of anorectum, and pruritus ani.

CONTRAINDICATIONS

Hydrocortisone acetate suppositories are contraindicated in those patients having a history of hypersensitivity to hydrocortisone acetate or any of the components.

PRECAUTIONS

Do not use hydrocortisone acetate suppositories unless adequate proctologic examination is made.

If irritation develops, the product should be discontinued and appropriate therapy instituted.

In the presence of an infection, the use of an appropriate antifungal or antibacterial agent should be instituted. If a favorable response does not occur promptly, hydrocortisone acetate should be discontinued until the infection has been adequately controlled.

Carcinogenesis

No long-term studies in animals have been performed to evaluate the carcinogenic potential of corticosteroid suppositories.

Pregnancy Category C

In laboratory animals, topical steroids have been associated with an increase in the incidence of fetal abnormalities when gestating females have been exposed to rather low dosage levels. There are no adequate and well-controlled studies in pregnant women.

Hydrocortisone acetate suppositories should only be used during pregnancy if the potential benefit justifies the risk of the fetus. Drugs of this class should not be used extensively on pregnant patients, in large amounts, or for prolonged periods of time.

It is not known whether this drug is excreted in human milk, and because many drugs are excreted in human milk and because of the potential for serious adverse reactions in nursing infants from hydrocortisone acetate suppositories, a decision should be made whether to discontinue nursing or to discontinue the drug, taking into account the importance of the drug to the mother.

ADVERSE REACTIONS

The following local adverse reactions have been reported with hydrocortisone acetate suppositories; burning, itching, irritation, dryness, folliculitis, hypopigmentation, allergic contact dermatitis, secondary infection.

To report an adverse event, please contact Cameron Pharmaceuticals, LLC at 1-888-767-7913.

Drug abuse and dependence have not been reported in patients treated with hydrocortisone acetate suppositories.

OVERDOSAGE

If signs and symptoms of systemic overdosage occur, discontinue use.

DOSAGE AND ADMINISTRATION

FOR RECTAL ADMINISTRATION. Detach one suppository from strip of suppositories. Hold suppository upright and carefully separate tabs at top opening and pull downward from the pointed end to expose the suppository. Remove the suppository from the pocket. Avoid excessive handling of suppository which is designed to melt at body temperature. Insert one suppository rectally, pointed end first. Insert one suppository in the rectum twice daily, morning and night for two weeks, in nonspecific proctitis. In more severe cases, one suppository three times a day or two suppositories twice daily. In factitial proctitis, the recommended duration of therapy is six to eight weeks or less, according to the response of the individual case.

HOW SUPPLIED

Hydrocortisone acetate suppositories 25mg are off-white, smooth surfaced and bullet shaped with one pointed end.

Box of 12 suppositories, NDC 42494-341-12

Box of 24 suppositories, NDC 42494-341-24

STORAGE

Store at 20°-25°C (68°-77°F) [See USP Controlled Room Temperature]. Excursions permitted to 15°-30°C (59°-86°F). Store away from heat. Protect from freezing. Avoid contact with eyes.

KEEP THIS AND ALL DRUGS OUT OF THE REACH OF CHILDREN. In case of accidental ingestion, seek professional assistance or contact a Poison Control Center immediately.

PHARMACIST

This product is not an Orange Book rated product, therefore all prescriptions using this product shall be subject to state and federal statutes as applicable. This product has not been subjected to FDA therapeutic or other equivalency testing. There are no claims of bioequivalence or therapeutic equivalence. Each person recommending a prescription substitution using this product shall make such recommendation based on his/her professional knowledge and opinion, upon evaluating the active ingredients, inactive ingredients, excipients and chemical information contained within the enclosed prescribing information.

Rx Only

Manufactured for:
Cameron Pharmaceuticals, LLC
Louisville, KY 40245

Rev. 08/21

Hydrocortisone Acetate Suppositories 25mg

FOR RECTAL USE ONLY

12/24 Suppositories
Unit Dose

Rx Only

2000003-01

PRINCIPAL DISPLAY PANEL - 25 mg Suppository Blister Pack Box

NDC 42494-341-12

CAMERON
PHARMACEUTICALS™

Hydrocortisone Acetate
Suppositories

25 mg

FOR RECTAL USE ONLY

12 Suppositories
Unit Dose

Rx Only